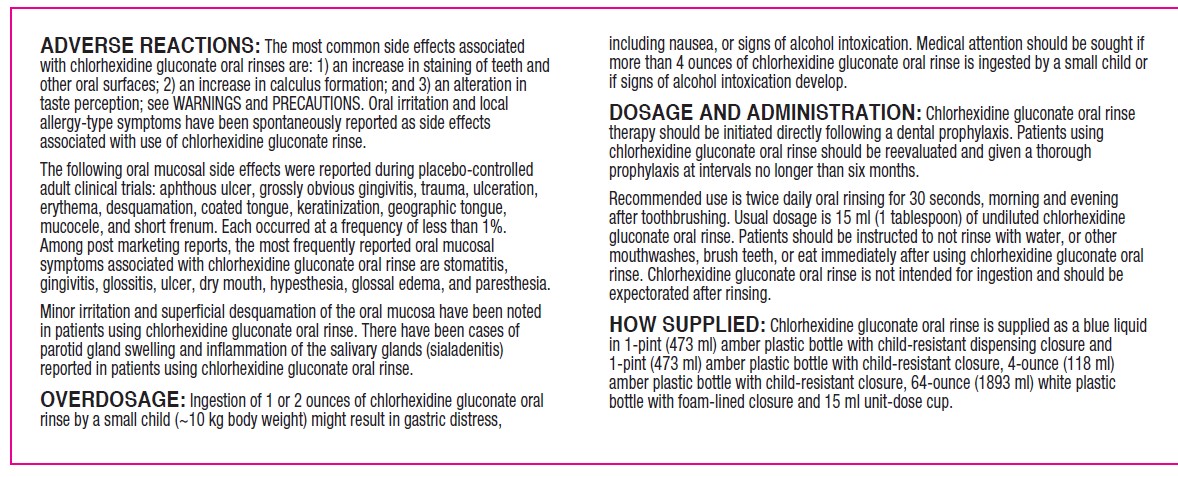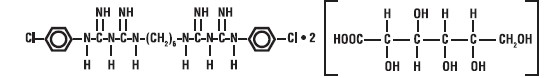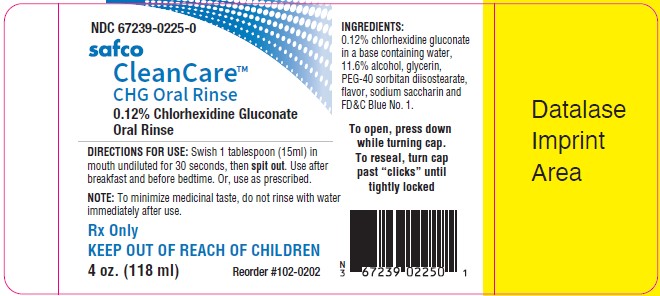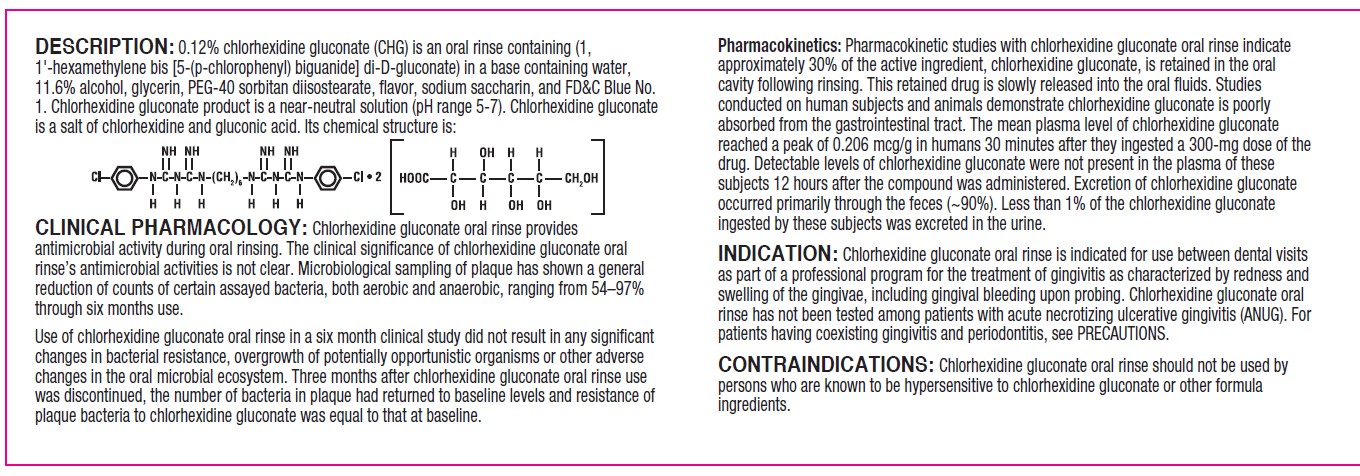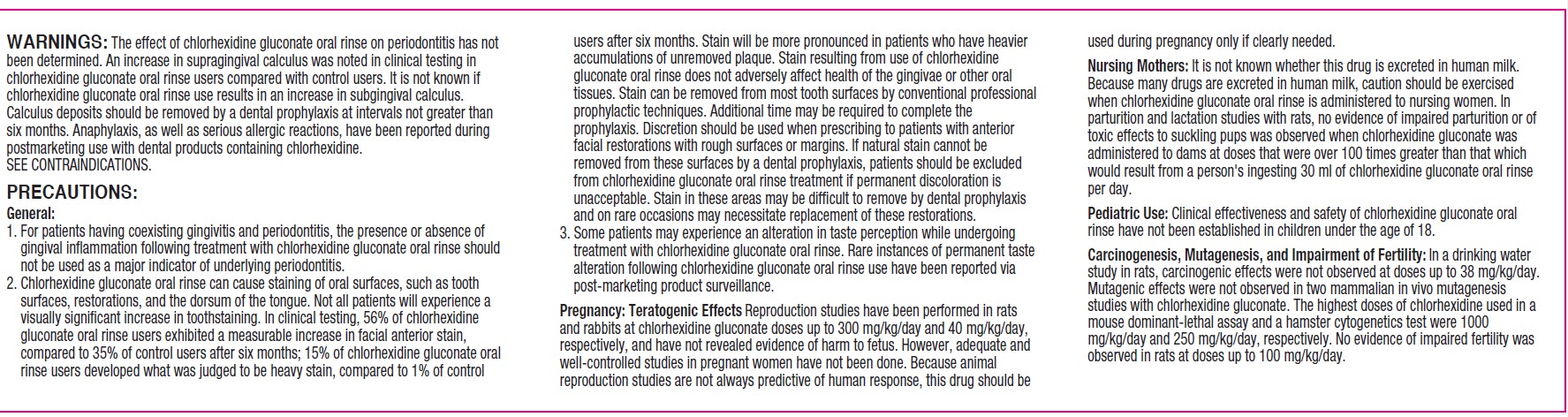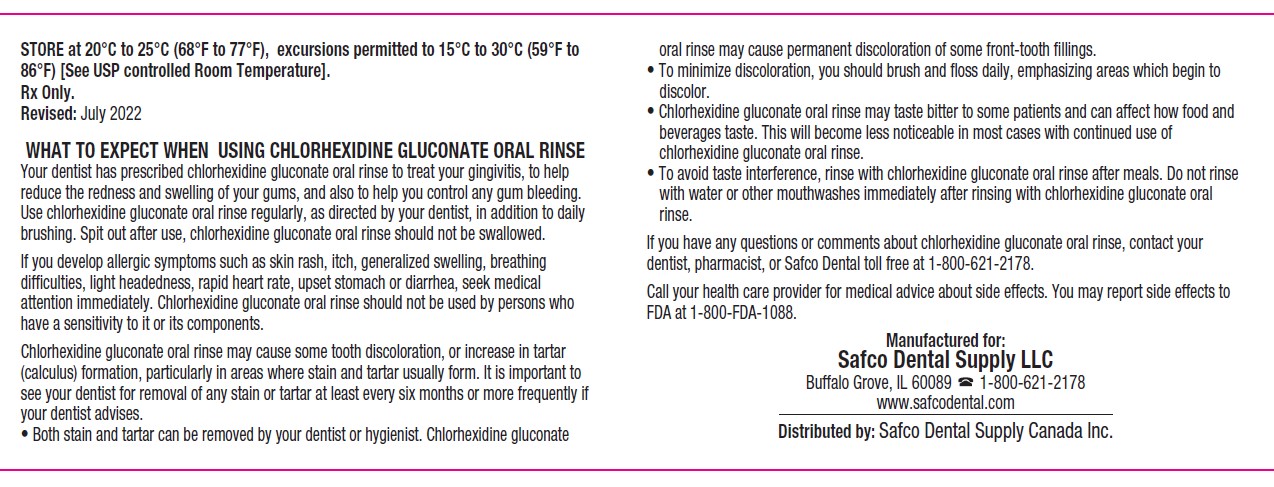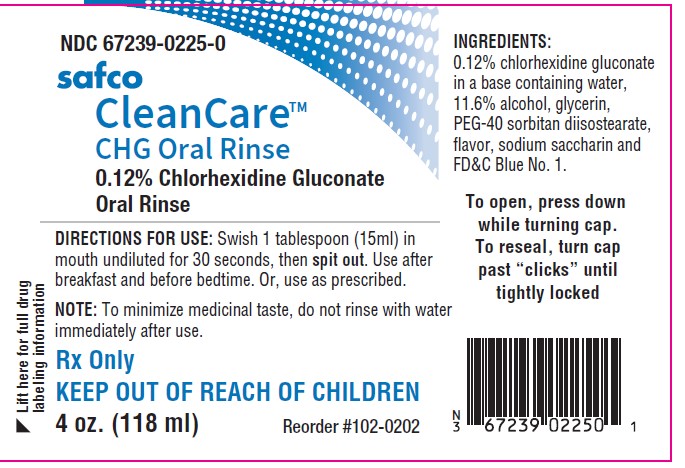 DRUG LABEL: CleanCare Chlorhexidine Gluconate 0.12% Oral Rinse
NDC: 67239-0225 | Form: SOLUTION
Manufacturer: Safco Dental Supply LLC
Category: prescription | Type: HUMAN PRESCRIPTION DRUG LABEL
Date: 20260302

ACTIVE INGREDIENTS: CHLORHEXIDINE GLUCONATE 1.2 mg/1 mL
INACTIVE INGREDIENTS: FD&C BLUE NO. 1; PEG-40 SORBITAN DIISOSTEARATE; WATER; GLYCERIN; ALCOHOL; SACCHARIN SODIUM

DESCRIPTION

DESCRIPTION:0.12% chlorhexidine gluconate (CHG) is an oral rinse containing (1,1'-hexamethylene bis [5-(p-chlorophenyl) biguanide] di-D-gluconate) in a base containing water, 11.6% alcohol, glycerin, PEG-40 sorbitan diisostearate, flavor, sodium saccharin, and FD&C Blue No. 1. Chlorhexidine gluconate product is a near-neutral solution (pH range 5-7). Chlorhexidine gluconate
is a salt of chlorhexidine and gluconic acid. Its chemical structure is:

CLINICAL PHARMACOLOGY

CLINICAL PHARMACOLOGY:Chlorhexidine gluconate oral rinse provides antimicrobial activity during oral rinsing. The clinical significance of chlorhexidine gluconate oral rinse’s antimicrobial activities is not clear. Microbiological sampling of plaque has shown a general reduction of counts of certain assayed bacteria, both aerobic and anaerobic, ranging from 54–97% through six months use.

Use of chlorhexidine gluconate oral rinse in a six month clinical study did not result in any significant changes in bacterial resistance, overgrowth of potentially opportunistic organisms or other adverse changes in the oral microbial ecosystem. Three months after chlorhexidine gluconate oral rinse use was discontinued, the number of bacteria in plaque had returned to baseline levels and resistance of plaque bacteria to chlorhexidine gluconate was equal to that at baseline.

PHARMACOKINETICS

Pharmacokinetics:Pharmacokinetic studies with chlorhexidine gluconate oral rinse indicate approximately 30% of the active ingredient, chlorhexidine gluconate, is retained in the oral cavity following rinsing. This retained drug is slowly released into the oral fluids. Studies
conducted on human subjects and animals demonstrate chlorhexidine gluconate is poorly absorbed from the gastrointestinal tract. The mean plasma level of chlorhexidine gluconate reached a peak of 0.206 mcg/g in humans 30 minutes after they ingested a 300-mg dose of the drug. Detectable levels of chlorhexidine gluconate were not present in the plasma of these subjects 12 hours after the compound was administered. Excretion of chlorhexidine gluconate occurred primarily through the feces (~90%). Less than 1% of the chlorhexidine gluconate ingested by these subjects was excreted in the urine.

INDICATIONS AND USAGE

INDICATION:Chlorhexidine gluconate oral rinse is indicated for use between dental visits as part of a professional program for the treatment of gingivitis as characterized by redness and swelling of the gingivae, including gingival bleeding upon probing. Chlorhexidine gluconate oral rinse has not been tested among patients with acute necrotizing ulcerative gingivitis (ANUG). For patients having coexisting gingivitis and periodontitis, see PRECAUTIONS.

CONTRAINDICATIONS

CONTRAINDICATIONS:Chlorhexidine gluconate oral rinse should not be used by persons who are known to be hypersensitive to chlorhexidine gluconate or other formula ingredients.

WARNINGS

WARNINGS:The effect of chlorhexidine gluconate oral rinse on periodontitis has not been determined. An increase in supragingival calculus was noted in clinical testing in chlorhexidine gluconate oral rinse users compared with control users. It is not known if chlorhexidine gluconate oral rinse use results in an increase in subgingival calculus. Calculus deposits should be removed by a dental prophylaxis at intervals not greater than six months. Anaphylaxis, as well as serious allergic reactions, have been reported during postmarketing use with dental products containing chlorhexidine.
SEE CONTRAINDICATIONS.

PRECAUTIONS:
General :

1. For patients having coexisting gingivitis and periodontitis, the presence or absence of gingival inflammation following treatment with chlorhexidine gluconate oral rinse should not be used as a major indicator of underlying periodontitis.
2. Chlorhexidine gluconate oral rinse can cause staining of oral surfaces, such as tooth surfaces, restorations, and the dorsum of the tongue. Not all patients will experience a visually significant increase in toothstaining. In clinical testing, 56% of chlorhexidine gluconate oral rinse users exhibited a measurable increase in facial anterior stain, compared to 35% of control users after six months; 15% of chlorhexidine gluconate oral rinse users developed what was judged to be heavy stain, compared to 1% of control users after six months. Stain will be more pronounced in patients who have heavier accumulations of unremoved plaque. Stain resulting from use of chlorhexidine gluconate oral rinse does not adversely affect health of the gingivae or other oral tissues. Stain can be removed from most tooth surfaces by conventional professional prophylactic techniques. Additional time may be required to complete the prophylaxis. Discretion should be used when prescribing to patients with anterior facial restorations with rough surfaces or margins. If natural stain cannot be removed from these surfaces by a dental prophylaxis, patients should be excluded from chlorhexidine gluconate oral rinse treatment if permanent discoloration is unacceptable. Stain in these areas may be difficult to remove by dental prophylaxis and on rare occasions may necessitate replacement of these restorations.
3. Some patients may experience an alteration in taste perception while undergoing treatment with chlorhexidine gluconate oral rinse. Rare instances of permanent taste alteration following chlorhexidine gluconate oral rinse use have been reported via post-marketing product surveillance.

PREGNANCY

Pregnancy: Teratogenic EffectsReproduction studies have been performed in rats and rabbits at chlorhexidine gluconate doses up to 300 mg/kg/day and 40 mg/kg/day, respectively, and have not revealed evidence of harm to fetus. However, adequate and
well-controlled studies in pregnant women have not been done. Because animal reproduction studies are not always predictive of human response, this drug should be used during pregnancy only if clearly needed.

NURSING MOTHERS

Nursing Mothers:It is not known whether this drug is excreted in human milk. Because many drugs are excreted in human milk, caution should be exercised when chlorhexidine gluconate oral rinse is administered to nursing women. In parturition and lactation studies with rats, no evidence of impaired parturition or of toxic effects to suckling pups was observed when chlorhexidine gluconate was administered to dams at doses that were over 100 times greater than that which would result from a person's ingesting 30 ml of chlorhexidine gluconate oral rinse per day.

PEDIATRIC USE

Pediatric Use:Clinical effectiveness and safety of chlorhexidine gluconate oral rinse have not been established in children under the age of 18.

CARCINOGENESIS AND MUTAGENESIS AND IMPAIRMENT OF FERTILITY

Carcinogenesis, Mutagenesis, and Impairment of Fertility:In a drinking water study in rats, carcinogenic effects were not observed at doses up to 38 mg/kg/day. Mutagenic effects were not observed in two mammalian in vivo mutagenesis studies with chlorhexidine gluconate. The highest doses of chlorhexidine used in a mouse dominant-lethal assay and a hamster cytogenetics test were 1000
mg/kg/day and 250 mg/kg/day, respectively. No evidence of impaired fertility was observed in rats at doses up to 100 mg/kg/day.

ADVERSE REACTIONS

ADVERSE REACTIONS:The most common side effects associated with chlorhexidine gluconate oral rinses are: 1) an increase in staining of teeth and other oral surfaces; 2) an increase in calculus formation; and 3) an alteration in taste perception; see WARNINGS and PRECAUTIONS. Oral irritation and local allergy-type symptoms have been spontaneously reported as side effects
associated with use of chlorhexidine gluconate rinse.

The following oral mucosal side effects were reported during placebo-controlled adult clinical trials: aphthous ulcer, grossly obvious gingivitis, trauma, ulceration, erythema, desquamation, coated tongue, keratinization, geographic tongue, mucocele, and short frenum. Each occurred at a frequency of less than 1%. Among post marketing reports, the most frequently reported oral mucosal symptoms associated with chlorhexidine gluconate oral rinse are stomatitis, gingivitis, glossitis, ulcer, dry mouth, hypesthesia, glossal edema, and paresthesia.

Minor irritation and superficial desquamation of the oral mucosa have been noted
in patients using chlorhexidine gluconate oral rinse. There have been cases of
parotid gland swelling and inflammation of the salivary glands (sialadenitis)
reported in patients using chlorhexidine gluconate oral rinse.

OVERDOSAGE

OVERDOSAGE:Ingestion of 1 or 2 ounces of chlorhexidine gluconate oral rinse by a small child (~10 kg body weight) might result in gastric distress, including nausea, or signs of alcohol intoxication. Medical attention should be sought if more than 4 ounces of chlorhexidine gluconate oral rinse is ingested by a small child or if signs of alcohol intoxication develop.

DOSAGE AND ADMINISTRATION:Chlorhexidine gluconate oral rinse therapy should be initiated directly following a dental prophylaxis. Patients using chlorhexidine gluconate oral rinse should be reevaluated and given a thorough prophylaxis at intervals no longer than six months.

Recommended use is twice daily oral rinsing for 30 seconds, morning and evening after toothbrushing. Usual dosage is 15 ml (1 tablespoon) of undiluted chlorhexidine gluconate oral rinse. Patients should be instructed to not rinse with water, or other mouthwashes, brush teeth, or eat immediately after using chlorhexidine gluconate oral rinse. Chlorhexidine gluconate oral rinse is not intended for ingestion and should be expectorated after rinsing.

HOW SUPPLIED

HOW SUPPLIED:Chlorhexidine gluconate oral rinse is supplied as a blue liquid in 1-pint (473 ml) amber plastic bottle with child-resistant dispensing closure and 1-pint (473 ml) amber plastic bottle with child-resistant closure, 4-ounce (118 ml) amber plastic bottle with child-resistant closure, 64-ounce (1893 ml) white plastic bottle with foam-lined closure and 15 ml unit-dose cup.

STORAGE AND HANDLING

STORE at 20°C to 25°C (68°F to 77°F), excursions permitted to 15°C to 30°C (59°F to
86°F) [See USP controlled Room Temperature].

OTHER SAFETY INFORMATION

Rx Only.
Revised: July 2022

WHAT TO EXPECT WHEN USING CHLORHEXIDINE GLUCONATE ORAL RINSE
Your dentist has prescribed chlorhexidine gluconate oral rinse to treat your gingivitis, to help reduce the redness and swelling of your gums, and also to help you control any gum bleeding. Use chlorhexidine gluconate oral rinse regularly, as directed by your dentist, in addition to daily brushing. Spit out after use, chlorhexidine gluconate oral rinse should not be swallowed.

If you develop allergic symptoms such as skin rash, itch, generalized swelling, breathing difficulties, light headedness, rapid heart rate, upset stomach or diarrhea, seek medical attention immediately. Chlorhexidine gluconate oral rinse should not be used by persons who have a sensitivity to it or its components.

Chlorhexidine gluconate oral rinse may cause some tooth discoloration, or increase in tartar (calculus) formation, particularly in areas where stain and tartar usually form. It is important to see your dentist for removal of any stain or tartar at least every six months or more frequently if your dentist advises.
• Both stain and tartar can be removed by your dentist or hygienist. Chlorhexidine gluconate oral rinse may cause permanent discoloration of some front-tooth fillings.
• To minimize discoloration, you should brush and floss daily, emphasizing areas which begin to discolor.
• Chlorhexidine gluconate oral rinse may taste bitter to some patients and can affect how food and beverages taste. This will become less noticeable in most cases with continued use of chlorhexidine gluconate oral rinse.
• To avoid taste interference, rinse with chlorhexidine gluconate oral rinse after meals. Do not rinse with water or other mouthwashes immediately after rinsing with chlorhexidine gluconate oral rinse.

If you have any questions or comments about chlorhexidine gluconate oral rinse, contact your dentist, pharmacist, or Safco Dental toll free at 1-800-621-2178.

Call your health care provider for medical advice about side effects. You may report side effects to FDA at 1-800-FDA-1088.

Manufactured for:
Safco Dental Supply LLC
Buffalo Grove, IL 60089 1-800-621-2178
www.safcodental.com
Distributed by:Safco Dental Supply Canada Inc.

INSTRUCTIONS FOR USE

DIRECTIONS FOR USE:Swish 1 tablespoon (15ml) in mouth undiluted for 30 seconds, then spit out. Use after breakfast and before bedtime. Or, use as prescribed. NOTE: To minimize medicinal taste, do not rinse with water immediately after use.

PACKAGE LABEL

NDC 67239-0225-0

safco CleanCareTMCHG Oral Rinse

0.12% Chlorhexidine Gluconate Oral Rinse

Lift here for full drug labeling information

DIRECTIONS FOR USE:Swish 1 tablespoon (15ml) in mouth undiluted for 30 seconds, then spit out. Use after breakfast and before bedtime. Or, use as prescribed.

NOTE:To minimize medicinal taste, do not rinse with water immediately after use.

Rx Only

KEEP OUT OF REACH OF CHILDREN

4 oz. (118 ml)

Reorder #102-0202

INGREDIENTS:
0.12% chlorhexidine gluconate in a base containing water, 11.6% alcohol, glycerin, PEG-40 sorbitan diisostearate, flavor, sodium saccharin and FD&C Blue No. 1.

To open, press down while turning cap. To reseal, turn cap past “clicks” until tightly locked